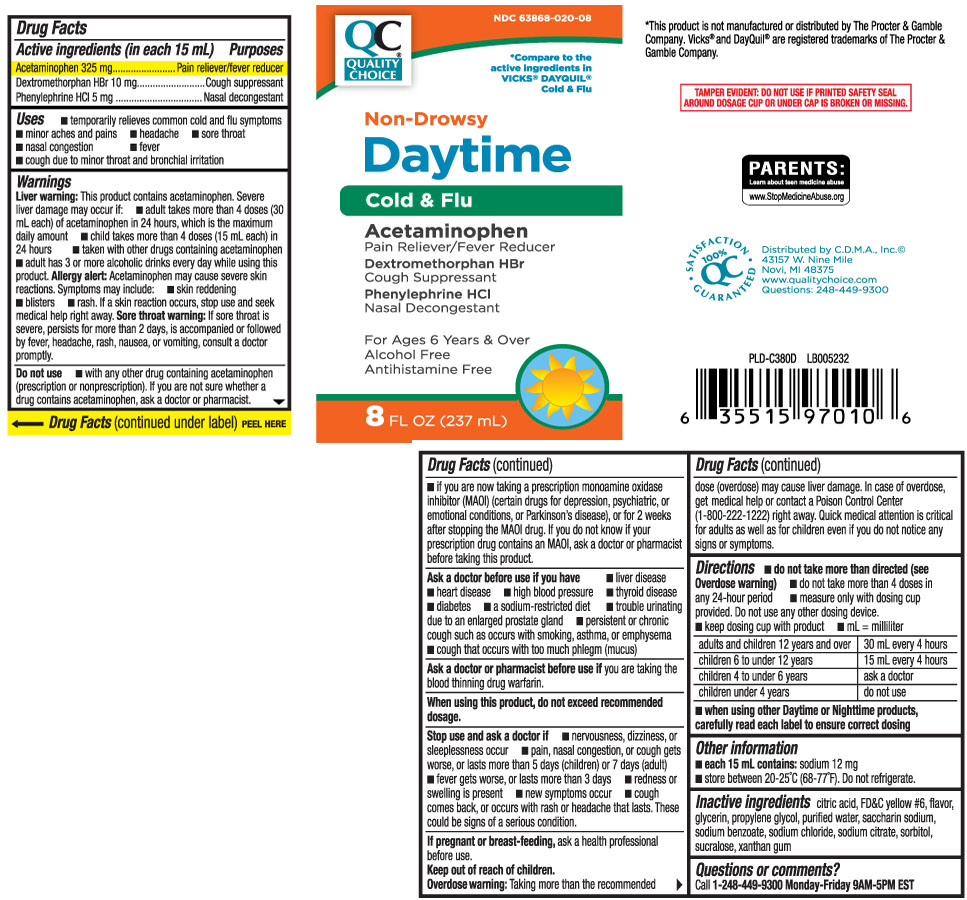 DRUG LABEL: Daytime Cold and Flu
NDC: 63868-020 | Form: LIQUID
Manufacturer: QUALITY CHOICE (Chain Drug Marketing Association)
Category: otc | Type: HUMAN OTC DRUG LABEL
Date: 20251216

ACTIVE INGREDIENTS: ACETAMINOPHEN 325 mg/15 mL; DEXTROMETHORPHAN HYDROBROMIDE 10 mg/15 mL; PHENYLEPHRINE HYDROCHLORIDE 5 mg/15 mL
INACTIVE INGREDIENTS: ANHYDROUS CITRIC ACID; FD&C YELLOW NO. 6; GLYCERIN; PROPYLENE GLYCOL; WATER; SACCHARIN SODIUM; TRISODIUM CITRATE DIHYDRATE; SODIUM BENZOATE; SODIUM CHLORIDE; SORBITOL; SUCRALOSE; XANTHAN GUM

Drug Facts

Active ingredients (in each 15 mL)

Acetaminophen 325 mg

Dextromethoprhan HBr 10 mg

Phenlyephrine HCl 5 mg

Purposes

Pain reliever/fever reducer

Cough suppressant

Nasal decongestant

Uses

- temporarily relieves these common cold/flu symptoms:
  - minor aches and pains
  - headache
  - sore throat
  - fever
  - nasal congestion
  - cough due to minor throat and bronchial irritation

Warnings

Liver warning: This product contains acetaminophen. Severe liver damage may occur if you take:

- adult takes more than 4 doses (30 mL each) of acetaminophen in 24 hours, which is the maximum daily amount
- child takes more than 4 doses (15 mL each) in 24 hours
- taken with other drugs containing acetaminophen
- adult has 3 or more alcoholic drinks every day while using this product

Allery alert: Acetaminophen may cause severe skin reactions. Symptoms may include:

- skin reddening
- blisters
- rash

If a skin reaction occurs, stop use and seek medical help right away

Sore throat warning: If sore throat is severe, persists for more than 2 days, is accompanied or followed by fever, headache, rash, nausea, or vomiting, consult a doctor promptly.

Do not use

- if you are now taking a prescription monoamine oxidase inhibitor (MAOI) (certain drugs for depression, psychiatric, or emotional conditions, or Parkinson's disease) or for 2 weeks after stopping the MAOI drug. If you do not know if your prescription drug contains an MAOI, ask a doctor or pharmacist before taking this product.
- with any other drug containing acetaminophen (prescription or non-prescription). If you are not sure whether a drug contains acetaminophen, ask a doctor or pharmacist.

Ask a doctor before use if you have

- liver disease
- heart disease
- thyroid disease
- diabetes
- high blood pressure
- a sodium-restricted diet
- persistent or chronic cough such as occurs with smoking, asthma or emphysema
- cough accompanied by excessive phlegm (mucus)
- trouble urinating due to an enlarged prostate gland

Ask a doctor or pharmacist before use if you are

taking the blood thinning drug warfarin.

When using this product,

do not exceed recommended dosage.

Stop use and ask a doctor if

- nervousness, dizziness, or sleeplessness occur
- pain, nasal congestion, or cough gets worse, or lasts more than 5 days (children) or 7 days (adult)
- fever gets worse, or lasts more than 3 days
- redness or swelling is present
- new symptoms occur
- cough comes back or occurs, with rash or headache that lasts.

These could be signs of a serious condition.

If pregnant or breast-feeding,

ask a health professional before use.

Keep out of reach of children.

Overdose warning: Taking more than the recommended dose (overdose) may cause liver damage. In case of overdose, get medical help or contact a Poison Control Center (1-800-222-1222) right away. Quick medical attention is critical for adults as well as for children even if you do not notice any signs or symptoms.

Directions

- do not take more than directed (see overdose warning)
- do not exceed 4 doses in any 24-hour period
- measure only with dosing cup provided. Do not use any other dosing device
- keep dosing cup with product
- mL=milliliter

adults and children 12 years and over | 30 mL every 4 hours
children 6 to under 12 years | 15 mL every 4 hours
children 4 to under 6 years | ask a doctor
children under 4 years | do not use

- When using Day Time and Night Time products, carefully read each label to ensure correct dosing

Other information

- each 15 mL contains: sodium 12 mg
- store between 20-25ºC (68-77ºF). Do not refrigerate.

Inactive ingredients

citric acid, FD&C yellow #6, flavor, glycerin, propylene glycol, purified water, saccharin sodium, sodium benzoate, sodium chloride, sodium citrate, sorbitol, sucralose, xanthan gum

Questions or comments?

Call 1-248-449-9300 Monday-Friday 9AM-5PM EST

Principal Display Panel

*Compare to the active ingredients in Vicks® DayQuil® Cold & Flu

Non-drowsy

Daytime

Cold & Flu

For ages 6 and over

Acetaminophen/ Pain reliever-fever reducer

Dextromethorphan HBr/cough suppressant

Phenylephrine HCl/Nasal decongestant

For Ages 6 Years & Over

Alcohol Free

Antihistamine Free

FL OZ (mL)

TAMPER EVIDENT: DO NOT USE IF PRINTED SAFETY SEAL AROUND DOSAGE CUP OR UNDER CAP IS BROKEN OR MISSING.

*This product is not manufactured or distributed by The Procter & Gamble Company.Vicks® and DayQuil® are registered trademarks of The Procter & Gamble Company.

Distributed by C.D.M.A. Inc.©

43157 W Nine Mile

Novi, MI 48375

www.qualitychoice.com

Package Label

QUALITY CHOICE Non-Drowsy Daytime Cold & Flu